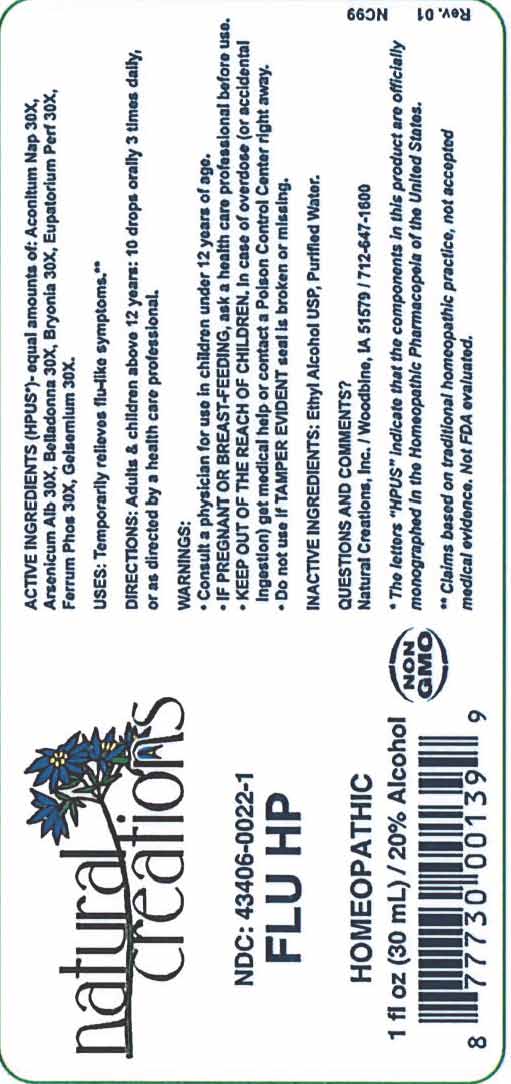 DRUG LABEL: FLU HP
NDC: 43406-0022 | Form: LIQUID
Manufacturer: Natural Creations, Inc.
Category: homeopathic | Type: HUMAN OTC DRUG LABEL
Date: 20251210

ACTIVE INGREDIENTS: ACONITUM NAPELLUS 30 [hp_X]/1 mL; ARSENIC TRIOXIDE 30 [hp_X]/1 mL; ATROPA BELLADONNA 30 [hp_X]/1 mL; BRYONIA ALBA ROOT 30 [hp_X]/1 mL; EUPATORIUM PERFOLIATUM FLOWERING TOP 30 [hp_X]/1 mL; FERRUM PHOSPHORICUM 30 [hp_X]/1 mL; GELSEMIUM SEMPERVIRENS ROOT 30 [hp_X]/1 mL
INACTIVE INGREDIENTS: WATER; ALCOHOL

FLU HP

ACTIVE INGREDIENT

ACTIVE INGREDIENTS (HPUS*) - eqaul amounts of: Aconitum Napellus 30X, Arsenicum Album 30X, Belladonna 30X, Bryonia Alba 30X, Eupatorium Perfoliatum 30X, Ferrum Phosphoricum 30X, Gelsemium Sempervirens 30X

INDICATIONS AND USAGE

USES: Temporarily relieves flu-like symptoms.**

WARNING:

- Consult a physician for use in children under 12 years of age.
- IF PREGNANT OR BREAST-FEEDING, ask a health care professional before use.
- KEEP OUT OF THE REACH OF CHILDREN. In case of overdose (or accidental ingestion) get medical help or contact a Poison Control Center right away.
- Do not use if TAMPER EVIDENT seal is broken or missing.

DOSAGE AND ADMINISTRATION

DIRECTIONS: Adults and children above 12 years: 10 drops orally 3 times daily, or as directed by a health care professional.

REFERENCES

* The letters "HPUS" indicate the components in the product are officially monographed in the Homeopathic Pharmacopeia of the United States.

**Claims based on traditional homeopathic practice, not accepted medical evidence. Not FDA evaluated.

INACTIVE INGREDIENTS: Purified Water, USP Ethanol Alcohol 20%

QUESTIONS AND COMMENTS?

Natural Creations / Woodbine, IA 51579 / 712-647-1600

PURPOSE

USES: Temporarily relieves flu-like symptoms.**

KEEP OUT OF REACH OF CHILDREN

KEEP OUT OF THE REACH OF CHILDREN. In case of overdose (or accidental ingestin) get medical help or contact a Poison Control Center.

PACKAGE LABEL

NDC: 43406-0022-1

FLU HP

HOMEOPATHIC

1 fl oz (30 mL) / 20% Alcohol